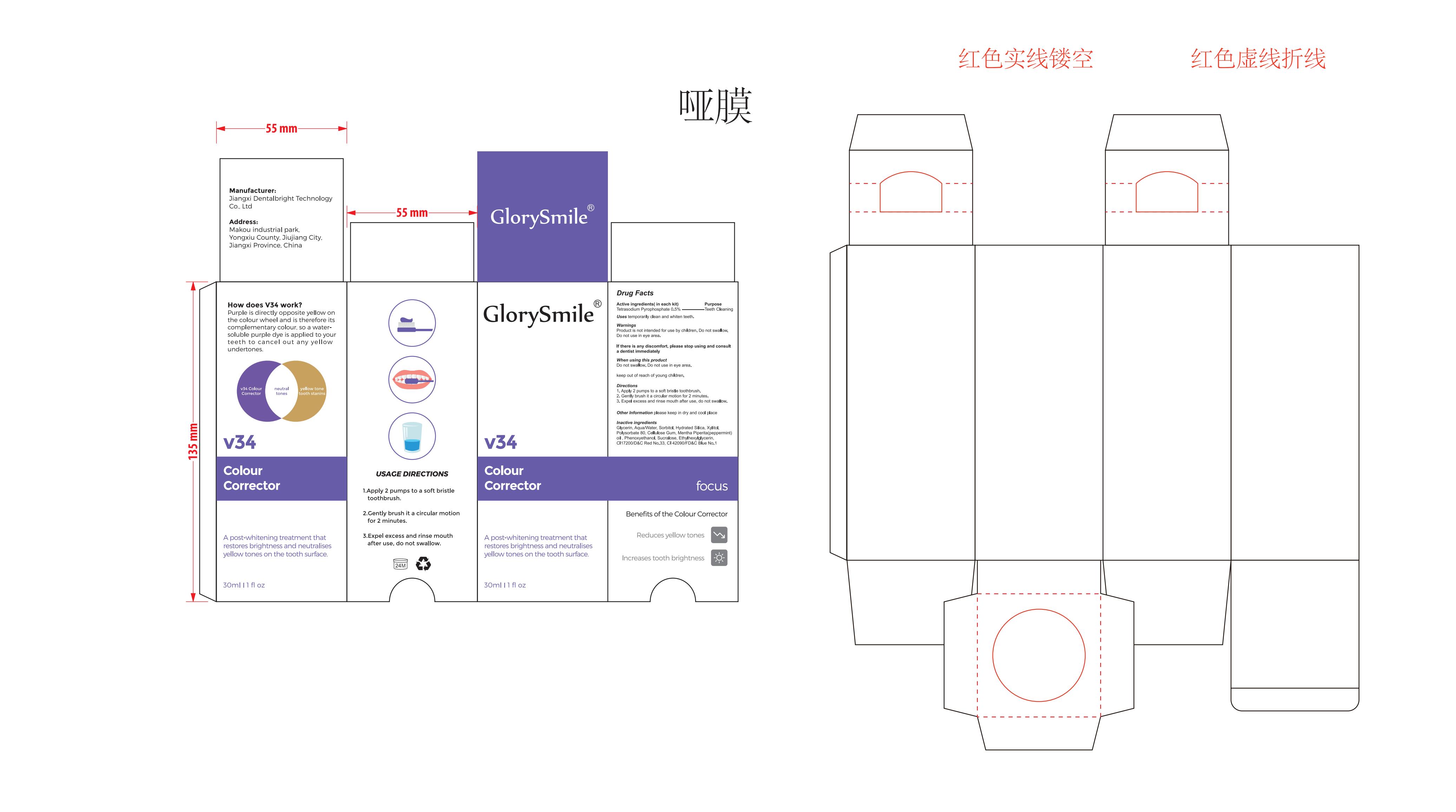 DRUG LABEL: V34 Colour Corrector
NDC: 83778-009 | Form: PASTE, DENTIFRICE
Manufacturer: Jiangxi Dentalbright Technology Co., Ltd
Category: otc | Type: HUMAN OTC DRUG LABEL
Date: 20250107

ACTIVE INGREDIENTS: SODIUM PYROPHOSPHATE 0.5 g/100 mL
INACTIVE INGREDIENTS: SORBITOL; FD&C BLUE NO. 1; ETHYLHEXYLGLYCERIN; D&C RED NO. 33; CARBOXYMETHYLCELLULOSE SODIUM, UNSPECIFIED FORM; GLYCERIN; WATER; HYDRATED SILICA; PEPPERMINT OIL; SUCRALOSE; PHENOXYETHANOL; XYLITOL; POLYSORBATE 80

83778-009 001Update

Active Ingredient

Tetrasodium Pyrophosphate

Purpose

Teeth cleaning

Use

Those who want to clean and whiten their teeth.

Warnings

Product is not intended for use by children. Do not swallow. Do not use in eye area.

Do not use

Product is not intended for use by children.

When Using

Do not swallow. Do not use in eye area.

Stop Use

If there is any discomfort, please stop using.

Ask Doctor

If there is any discomfort, please consult a dentist immediately

Keep Oot Of Reach Of Children

keep out of reach of young children

Directions

1. Apply 2 pumps to a soft bristle toothbrush.
2. Gently brush it a circular motion for 2 minutes.
3. Expel excess and rinse mouth after use, do not swallow.

Other information

please keep in dry and cool place

Inactive ingredients

Glycerin、Aqua/Water、Sorbitol、Hydrated Silica、Xylitol、Polysorbate 80、Cellulose Gum、Mentha Piperita(peppermint) oil 、Phenoxyethanol、Sucralose、Ethylhexylglycerin、CI17200/D&C Red No.33、CI 42090/FD&C Blue No.1